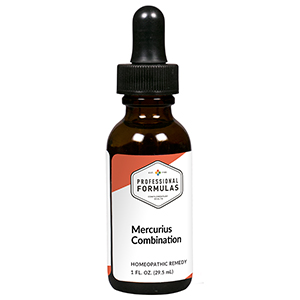 DRUG LABEL: Mercurius Combination
NDC: 63083-9233 | Form: LIQUID
Manufacturer: Professional Complementary Health Formulas
Category: homeopathic | Type: HUMAN OTC DRUG LABEL
Date: 20190815

ACTIVE INGREDIENTS: AILANTHUS ALTISSIMA FLOWERING TWIG 3 [hp_X]/29.5 mL; ECHINACEA ANGUSTIFOLIA WHOLE 3 [hp_X]/29.5 mL; AMARYLLIS BELLADONNA WHOLE 4 [hp_X]/29.5 mL; PHYTOLACCA AMERICANA ROOT 4 [hp_X]/29.5 mL; CALCIUM SULFIDE 8 [hp_X]/29.5 mL; DAPHNE MEZEREUM BARK 9 [hp_X]/29.5 mL; ARSENIC TRIOXIDE 12 [hp_X]/29.5 mL; HUMAN HERPESVIRUS 1 12 [hp_X]/29.5 mL; RECOMBINANT VARICELLA ZOSTER VIRUS GLYCOPROTEIN E ANTIGEN 12 [hp_X]/29.5 mL; LACHESIS MUTA VENOM 12 [hp_X]/29.5 mL; MERCURIUS SOLUBILIS 12 [hp_X]/29.5 mL
INACTIVE INGREDIENTS: ALCOHOL; WATER

R233

ACTIVE INGREDIENTS

Ailanthus glandulosus 3X
Echinacea angustifolia 3X
Belladonna 4X
Phytolacca decandra 4X
Hepar sulphuris calcareum 8X
Mezereum 9X
Arsenicum album 12X
Herpes simplex 12X
Herpes zoster 12X
Lachesis mutus 12X
Mercurius solubilis 12X

QUESTIONS

Professional Formulas

PO Box 2034 Lake Oswego, OR 97035

INDICATIONS

For the temporary relief of acne, boils, or red, itchy, irritated skin.*

PURPOSE

*Claims based on traditional homeopathic practice, not accepted medical evidence. Not FDA evaluated.

WARNINGS

Consult a doctor if condition worsens or if symptoms persist. Keep out of the reach of children. In case of overdose, get medical help or contact a poison control center right away. If pregnant or breastfeeding, ask a healthcare professional before use.

Keep out of the reach of children.

PREGNANCY OR BREAST FEEDING

If pregnant or breastfeeding, ask a healthcare professional before use.

DIRECTIONS

Place drops under tongue 30 minutes before/after meals. Adults and children 12 years and over: Take 10 drops up to 3 times per day. Consult a physician for use in children under 12 years of age.

OTHER INFORMATION

Tamper resistant. If seal is broken, do not use. After opening, close container tightly and store at room temperature away from heat.

INACTIVE INGREDIENTS

40% ethanol, purified water.

LABEL

Est 1985

Professional Formulas

Complementary Health

Mercurius Combination

Homeopathic Remedy

1 FL. OZ. (29.5 mL)